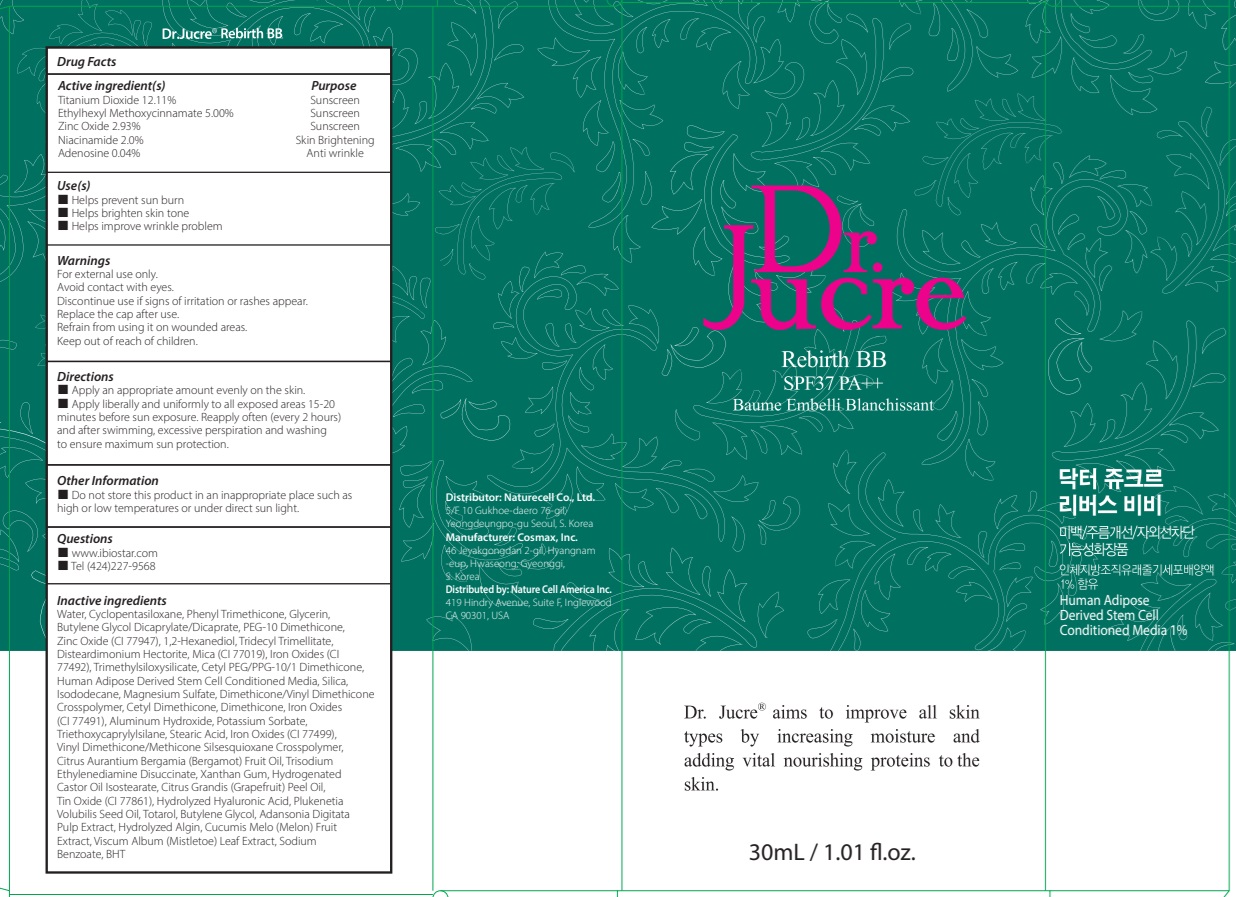 DRUG LABEL: Dr.Jucre Rebirth BB
NDC: 83071-100 | Form: CREAM
Manufacturer: NATURECELL CO., LTD.
Category: otc | Type: HUMAN OTC DRUG LABEL
Date: 20250102

ACTIVE INGREDIENTS: TITANIUM DIOXIDE 12.11 g/100 mL; OCTINOXATE 5 g/100 mL; ZINC OXIDE 2.93 g/100 mL; NIACINAMIDE 2 g/100 mL; ADENOSINE 0.04 g/100 mL
INACTIVE INGREDIENTS: WATER; CYCLOMETHICONE 5; PHENYL TRIMETHICONE

ACTIVE INGREDIENTS

Titanium Dioxide 12.11%
Ethylhexyl Methoxycinnamate 5.00%
Zinc Oxide 2.93%
Niacinamide 2.0%
Adenosine 0.04%

INACTIVE INGREDIENTS

Water, Cyclopentasiloxane, Phenyl Trimethicone, Glycerin, Butylene Glycol Dicaprylate/Dicaprate, PEG-10 Dimethicone, Zinc Oxide (CI 77947), 1,2-Hexanediol, Tridecyl Trimellitate, Disteardimonium Hectorite, Mica (CI 77019), Iron Oxides (CI 77492), Trimethylsiloxysilicate, Cetyl PEG/PPG-10/1 Dimethicone, Human Adipose Derived Stem Cell Conditioned Media, Silica, Isododecane, Magnesium Sulfate, Dimethicone/Vinyl Dimethicone Crosspolymer, Cetyl Dimethicone, Dimethicone, Iron Oxides (CI 77491), Aluminum Hydroxide, Potassium Sorbate, Triethoxycaprylylsilane, Stearic Acid, Iron Oxides (CI 77499), Vinyl Dimethicone/Methicone Silsesquioxane Crosspolymer, Citrus Aurantium Bergamia (Bergamot) Fruit Oil, Trisodium Ethylenediamine Disuccinate, Xanthan Gum, Hydrogenated Castor Oil Isostearate, Citrus Grandis (Grapefruit) Peel Oil, Tin Oxide (CI 77861), Hydrolyzed Hyaluronic Acid, Plukenetia Volubilis Seed Oil, Totarol, Butylene Glycol, Adansonia Digitata Pulp Extract, Hydrolyzed Algin, Cucumis Melo (Melon) Fruit Extract, Viscum Album (Mistletoe) Leaf Extract, Sodium Benzoate, BHT

PURPOSE

Sunscreen
Sunscreen
Sunscreen
Skin Brightening
Anti wrinkle

WARNINGS

For external use only.
Avoid contact with eyes.
Discontinue use if signs of irritation or rashes appear.
Replace the cap after use.
Refrain from using it on wounded areas.
Keep out of reach of children.

KEEP OUT OF REACH OF CHILDREN

Keep out of the reach of children.

Uses

■ Helps prevent sun burn
■ Helps brighten skin tone
■ Helps improve wrinkle problem

Directions

■ Apply an appropriate amount evenly on the skin.
■ Apply liberally and uniformly to all exposed areas 15-20 minutes before sun exposure. Reapply often (every 2 hours) and after swimming, excessive perspiration and washing to ensure maximum sun protection.

Other Information

■ Do not store this product in an inappropriate place such as high or low temperatures or under direct sun light.

Questions

■ www.ibiostar.com
■ Tel (424)227-9568